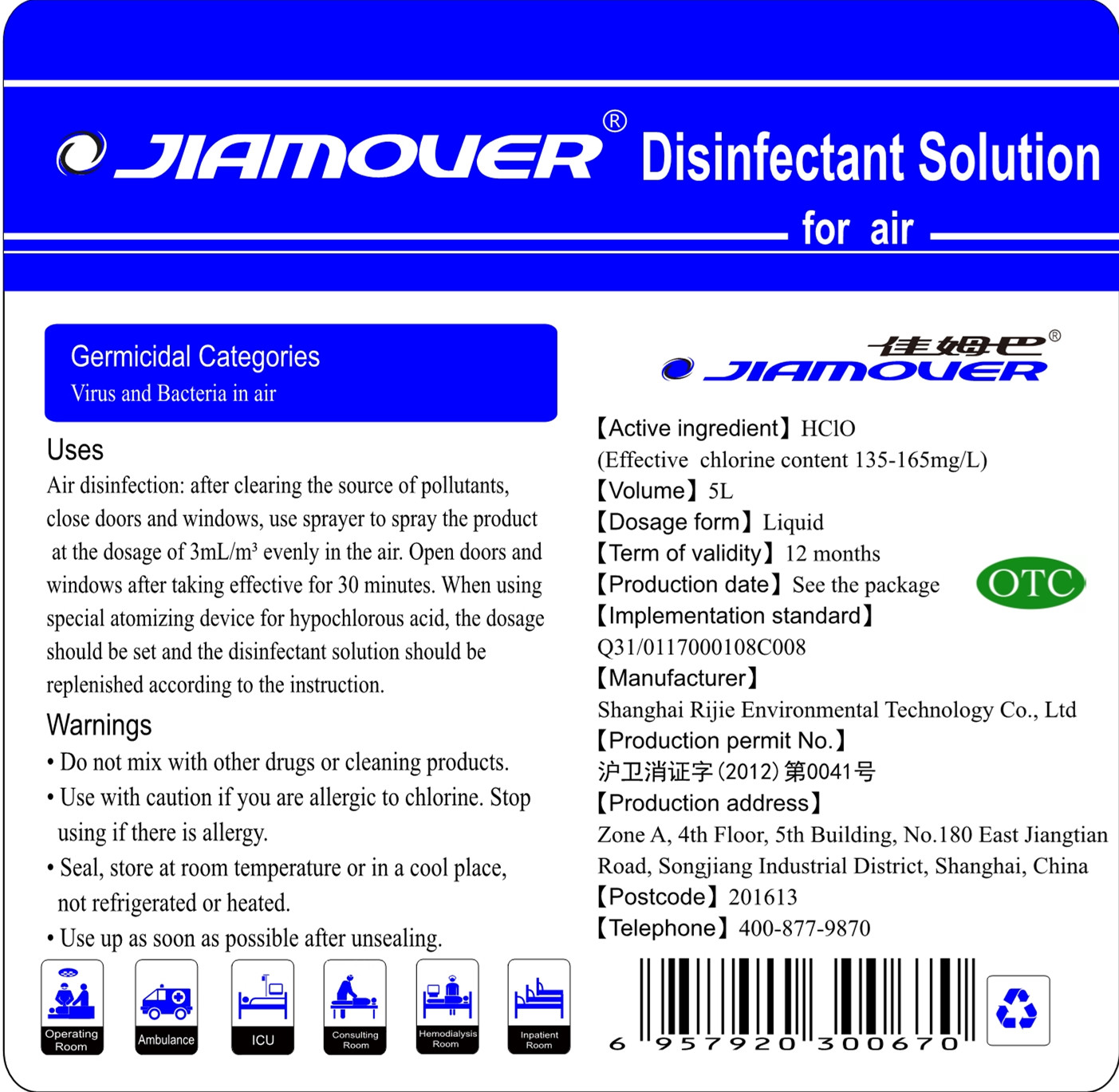 DRUG LABEL: Disinfectant Solution for air
NDC: 54125-006 | Form: LIQUID
Manufacturer: Shanghai Rijie Environmental Technology Co., Ltd
Category: otc | Type: HUMAN OTC DRUG LABEL
Date: 20200428

ACTIVE INGREDIENTS: HYPOCHLOROUS ACID 0.75 g/5000 mL
INACTIVE INGREDIENTS: WATER

DOSAGE AND ADMINISTRATION

Seal, store at room temperature or in a cool place,not refrigerated or heated.

INACTIVE INGREDIENT

purified water

INDICATIONS AND USAGE

Air disinfection: after clearing the source of pollutants,close doors and windows, use sprayer to spray the product at the dosage of 3mL/m3 evenly in the air. Open doors and windows after taking effective for 30 minutes. When using special atomizing device for hypochlorous acid, the dosage should be set and the disinfectant solution should be replenished according to the instruction.

ACTIVE INGREDIENT

hypochlorous acid

keep out of children

PURPOSE

Disinfection
Sterilization

WARNINGS

1.Do not mix with other drugs or cleaning products.
2.Use with caution if you are alergie to chlorine. Stop using if there is allergy.
3.Seal, store at room temperature or in a cool place,not refrigerated or heated.
4.Use up as soon as possible after unsealing.